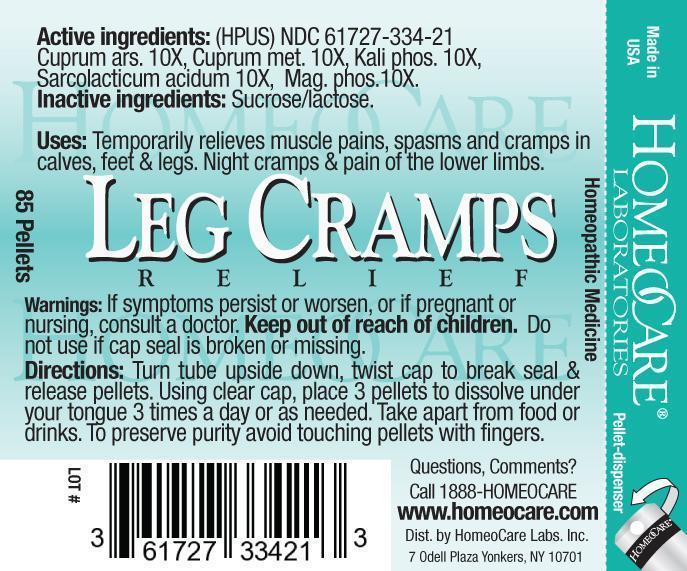 DRUG LABEL: Leg Cramps Relief
NDC: 61727-334 | Form: PELLET
Manufacturer: Homeocare Laboratories
Category: homeopathic | Type: HUMAN OTC DRUG LABEL
Date: 20181231

ACTIVE INGREDIENTS: CUPRIC ARSENITE 10 [hp_X]/4 g; COPPER 10 [hp_X]/4 g; POTASSIUM PHOSPHATE, DIBASIC 10 [hp_X]/4 g; LACTIC ACID, L- 10 [hp_X]/4 g; MAGNESIUM PHOSPHATE, TRIBASIC, PENTAHYDRATE 10 [hp_X]/4 g
INACTIVE INGREDIENTS: SUCROSE; LACTOSE

Leg Cramps Relief

Active Ingredients:(HPUS)

Cuprum Ars. 10X, Cuprum met. 10X, Kali phos.10X, Sarcolacticum acidum 10X, Mag. phos. 10X.

Purpose:

Temporarily relieves muscle pains, spasms and cramps in calves, feet & legs. Night cramps & pain of the lower limbs.

Keep out of reach of children.

Indications & Usage:

Temporarily relieves muscle pains, spasms and cramps in calves, feet & legs. Night cramps & pain of the lower limbs.

Warnings:

If symptoms persist or worsen, or if pregnant or nursing, consult a doctor. Keep out of reach of children. Do not use if cap seal is broken or missing.

Inactive Ingredients:

Sucrose/lactose.

Dosage and Administration:

Turn tube upside down, twist cap to break seal & release pellets. Using clear cap, place 3 pellets to dissolve under your tongue 3 times a day or as needed. Take apart from food or drinks. To preserve purity avoid touching pellets with fingers.

Leg Cramps Relief

Homeopathic Medicine

85 Pellets
hcl_label_legcramps-2012.jpg